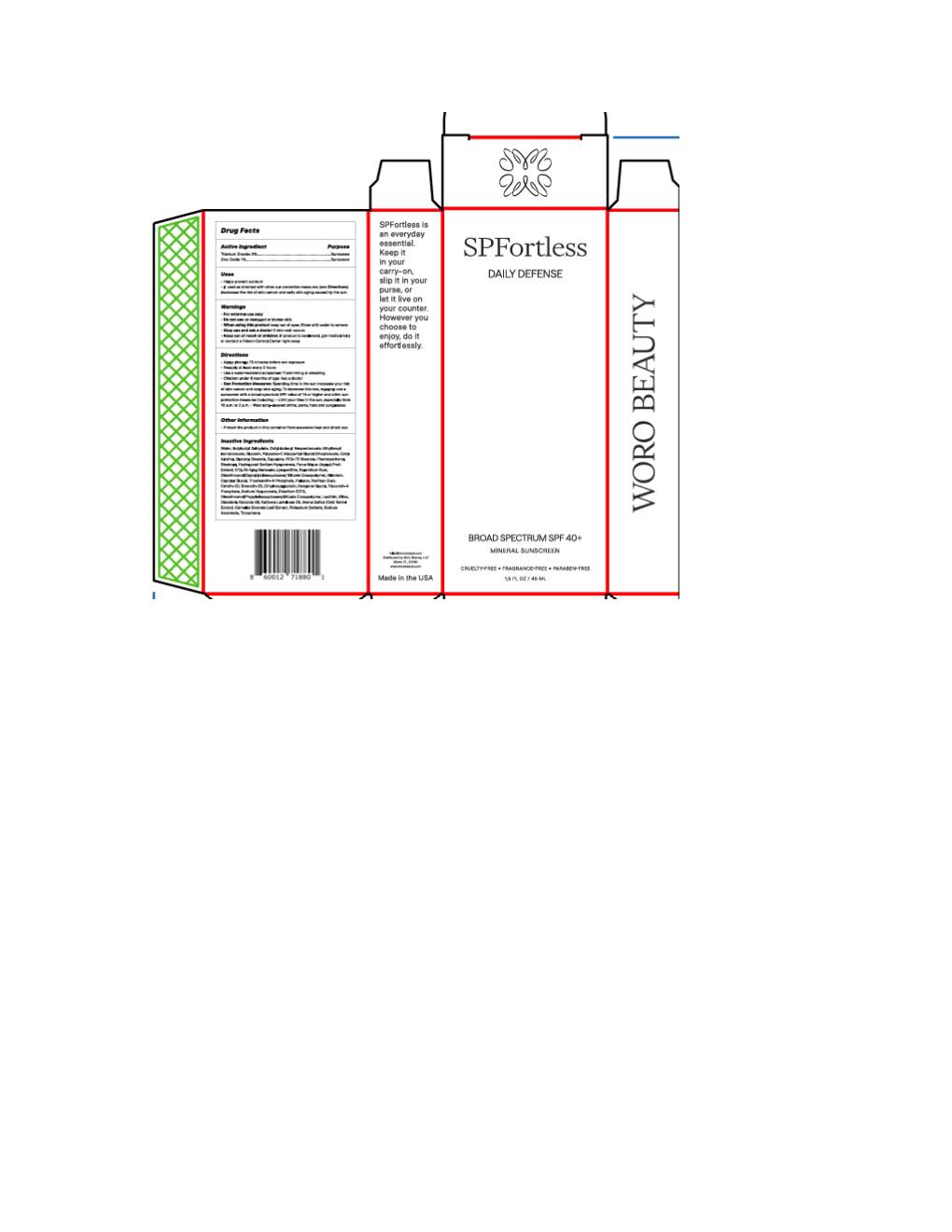 DRUG LABEL: Woro Beauty SPFortless
NDC: 84416-391 | Form: LOTION
Manufacturer: Woro Beauty
Category: otc | Type: HUMAN OTC DRUG LABEL
Date: 20251117

ACTIVE INGREDIENTS: TITANIUM DIOXIDE 19.4 mg/1 mL; ZINC OXIDE 9.7 mg/1 mL
INACTIVE INGREDIENTS: DIMETHICONOL/PROPYLSILSESQUIOXANE/SILICATE CROSSPOLYMER (450000000 MW); LECITHIN, SOYBEAN; SILICON DIOXIDE; ETHYLHEXYL ISONONANOATE; CETETH-20; POTASSIUM SORBATE; TOCOPHEROL; RUTTNERA LAMELLOSA OIL; POLYESTER-7; GLYCERIN; NEOPENTYL GLYCOL DIHEPTANOATE; DISODIUM EDTA-COPPER; CAMELLIA SINENSIS WHOLE; BUTYLOCTYL SALICYLATE; TRICETEARETH-4 PHOSPHATE; PULLULAN; XANTHAN GUM; STEARETH-20; HEXYLENE GLYCOL; TRILAURETH-4 PHOSPHATE; SODIUM ASCORBATE; OCTYLDODECYL NEOPENTANOATE; CETYL ALCOHOL; SQUALANE; PEG-75 STEARATE; PHENOXYETHANOL; .ALPHA.-BISABOLOL, (+)-; ETHYLHEXYLGLYCERIN; GLYCERYL STEARATE SE; ALKYL (C12-15) BENZOATE; ALLANTOIN; CAPRYLYL GLYCOL; AVENA SATIVA WHOLE; DICRATERIA ROTUNDA OIL

Woro Beauty SPFortless